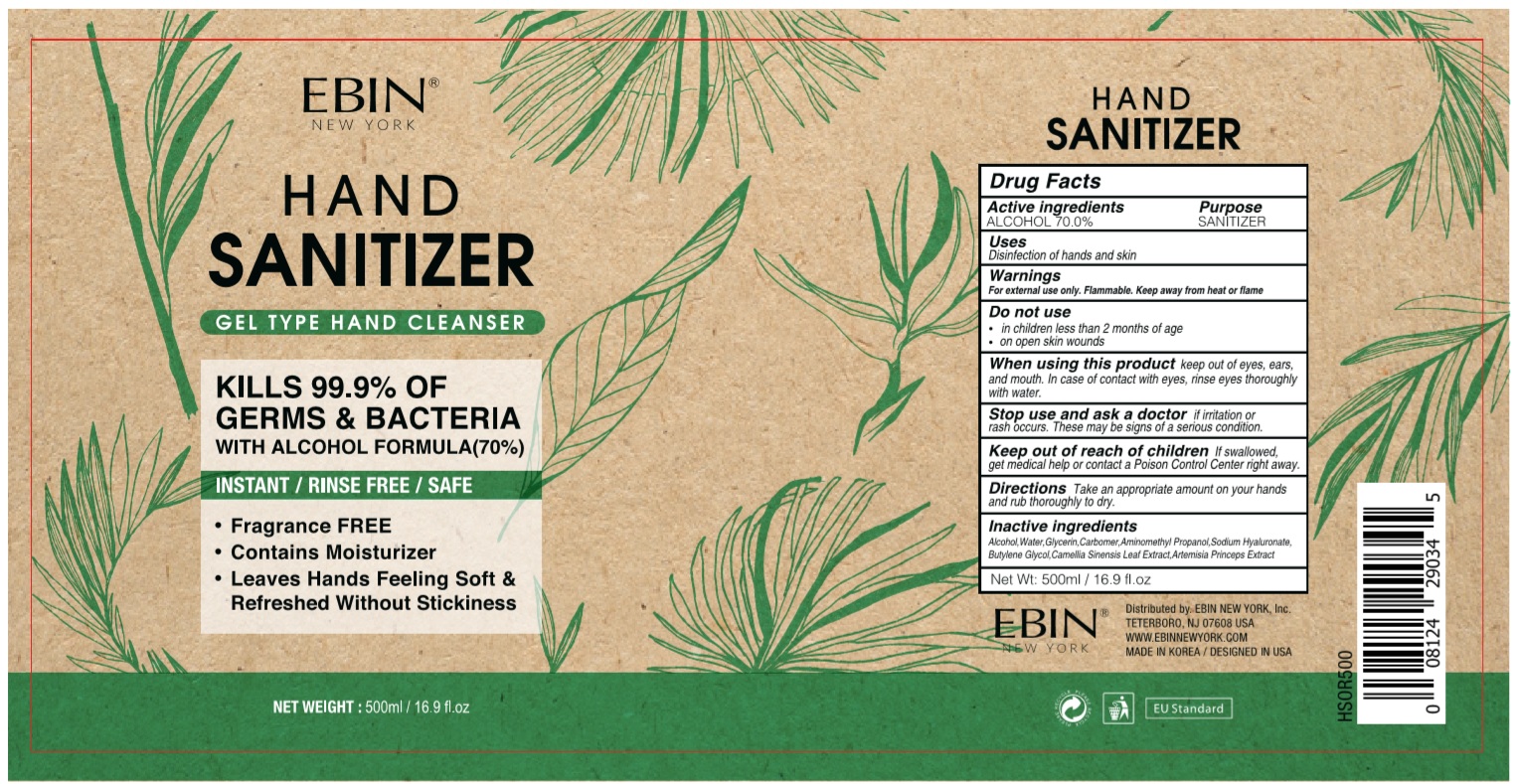 DRUG LABEL: EBIN NEW YORK HAND SANITIZER
NDC: 73823-570 | Form: GEL
Manufacturer: WHAIN COSMETIC
Category: otc | Type: HUMAN OTC DRUG LABEL
Date: 20200424

ACTIVE INGREDIENTS: ALCOHOL 350 mL/500 mL
INACTIVE INGREDIENTS: AMINOMETHYL PROPANEDIOL; GLYCERIN; HYALURONATE SODIUM; BUTYLENE GLYCOL; CARBOMER HOMOPOLYMER, UNSPECIFIED TYPE; WATER; ARTEMISIA PRINCEPS LEAF; GREEN TEA LEAF

[EBIN NEW YORK HAND SANITIZER ] 1 * 500 ml < Box : 73823-570-01